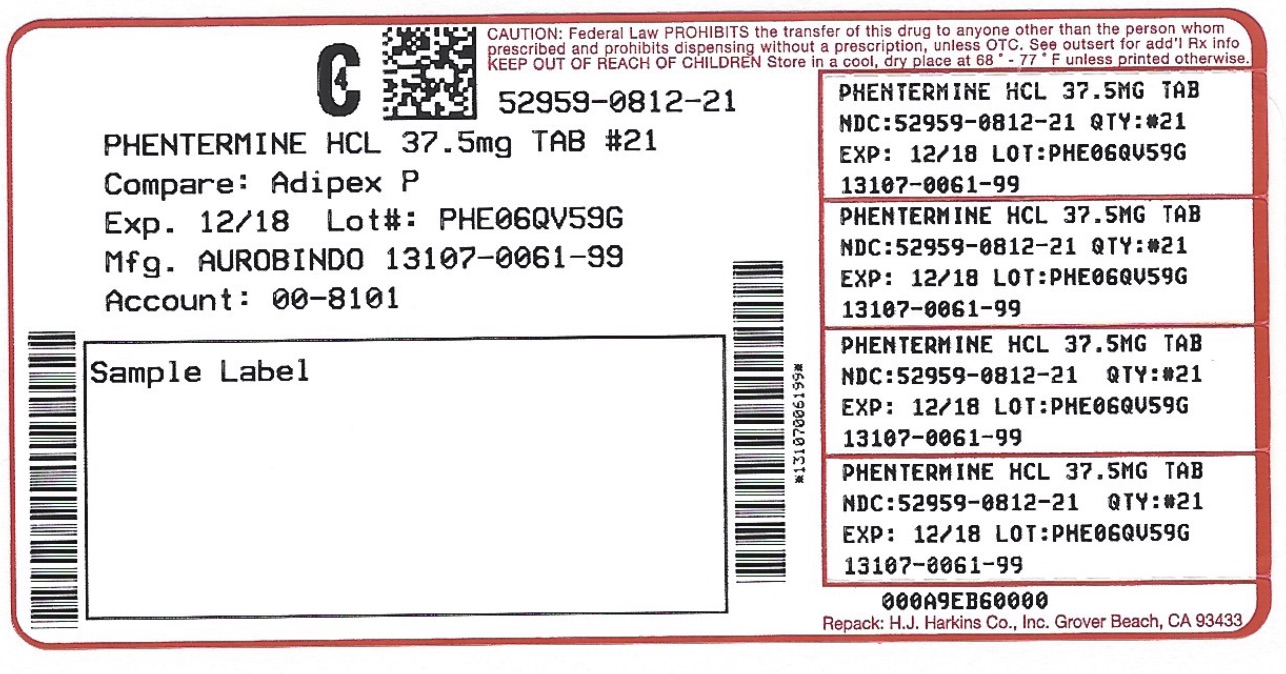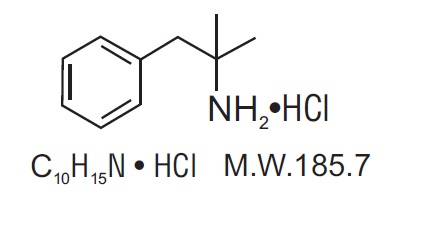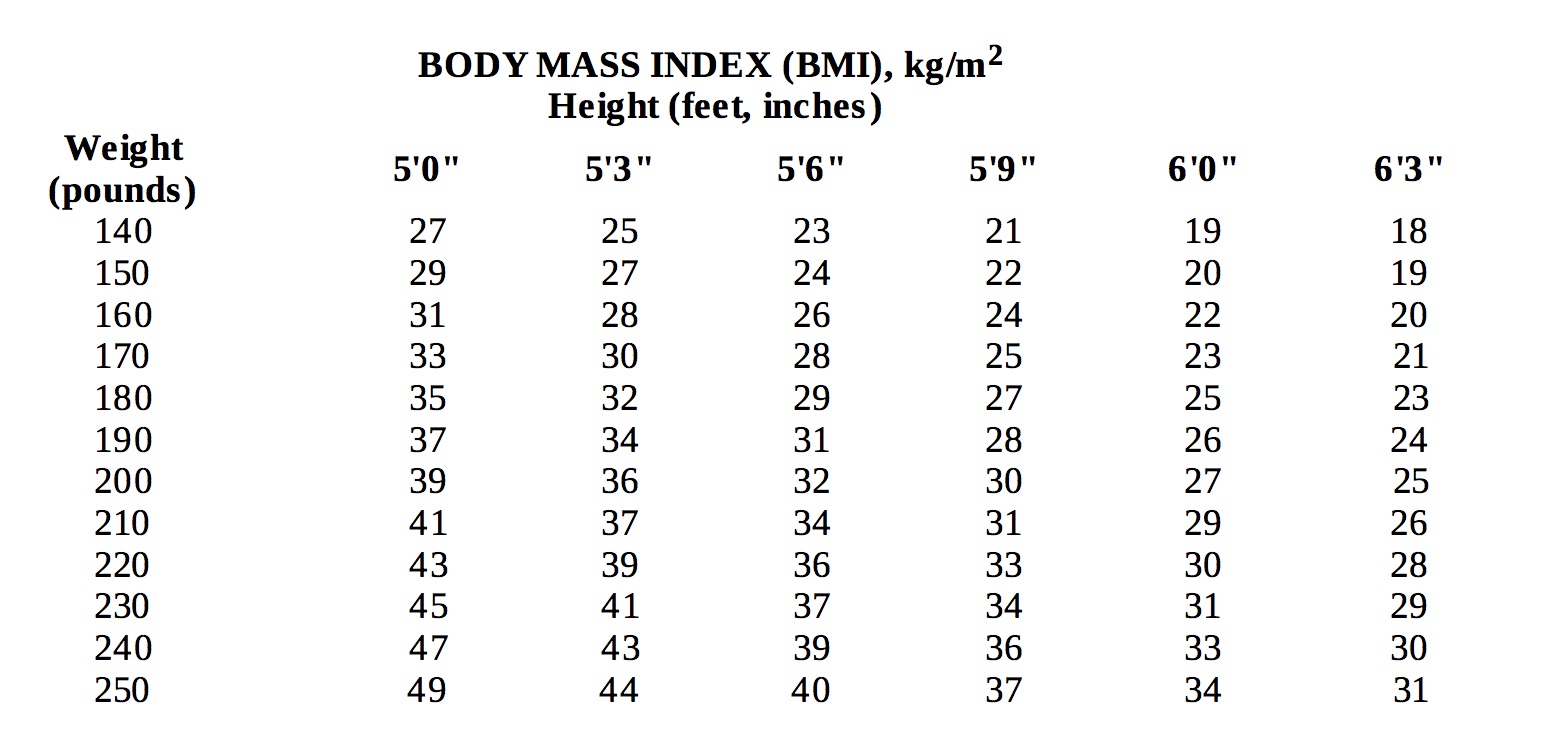 DRUG LABEL: Phentermine Hydrochloride
NDC: 52959-812 | Form: TABLET
Manufacturer: H.J. Harkins Company, Inc.
Category: prescription | Type: HUMAN PRESCRIPTION DRUG LABEL
Date: 20180103
DEA Schedule: CIV

ACTIVE INGREDIENTS: PHENTERMINE HYDROCHLORIDE 37.5 mg/1 1

Indications & Usage

Phentermine hydrochloride tablets USP are indicated as a short-term (a few weeks) adjunct in a regimen

of weight reduction based on exercise, behavioral modification and caloric restriction in the

management of exogenous obesity for patients with an initial body mass index greater than or equal to

30 kg/m , or greater than or equal to 27 kg/m in the presence of other risk factors (e.g., controlled

hypertension, diabetes, hyperlipidemia).
Below is a chart of body mass index (BMI) based on various heights and weights.

BMI is calculated by taking the patient's weight, in kilograms (kg), divided by the patient's height, in meters (m), squared. Metric conversions are as follows: pounds ÷ 2.2 = kg; inches x 0.0254 = meters.

Description

Phentermine hydrochloride USP is a sympathomimetic amine anorectic. Its chemical name is a,a- dimethylphenethylamine hydrochloride. The structural formula is as follows:

Phentermine hydrochloride USP is a white, odorless, hygroscopic, crystalline powder which is soluble in water and lower alcohols, slightly soluble in chloroform and insoluble in ether.

Phentermine hydrochloride tablets USP are available as an oral tablet containing 37.5 mg of phentermine hydrochloride USP (equivalent to 30 mg of phentermine base). Each phentermine hydrochloride tablet USP also contains the inactive ingredients microcrystalline cellulose, pregelatinized starch, anhydrous lactose, crospovidone, colloidal silicon dioxide, magnesium stearate, sucrose, corn starch and FD&C Blue #1.